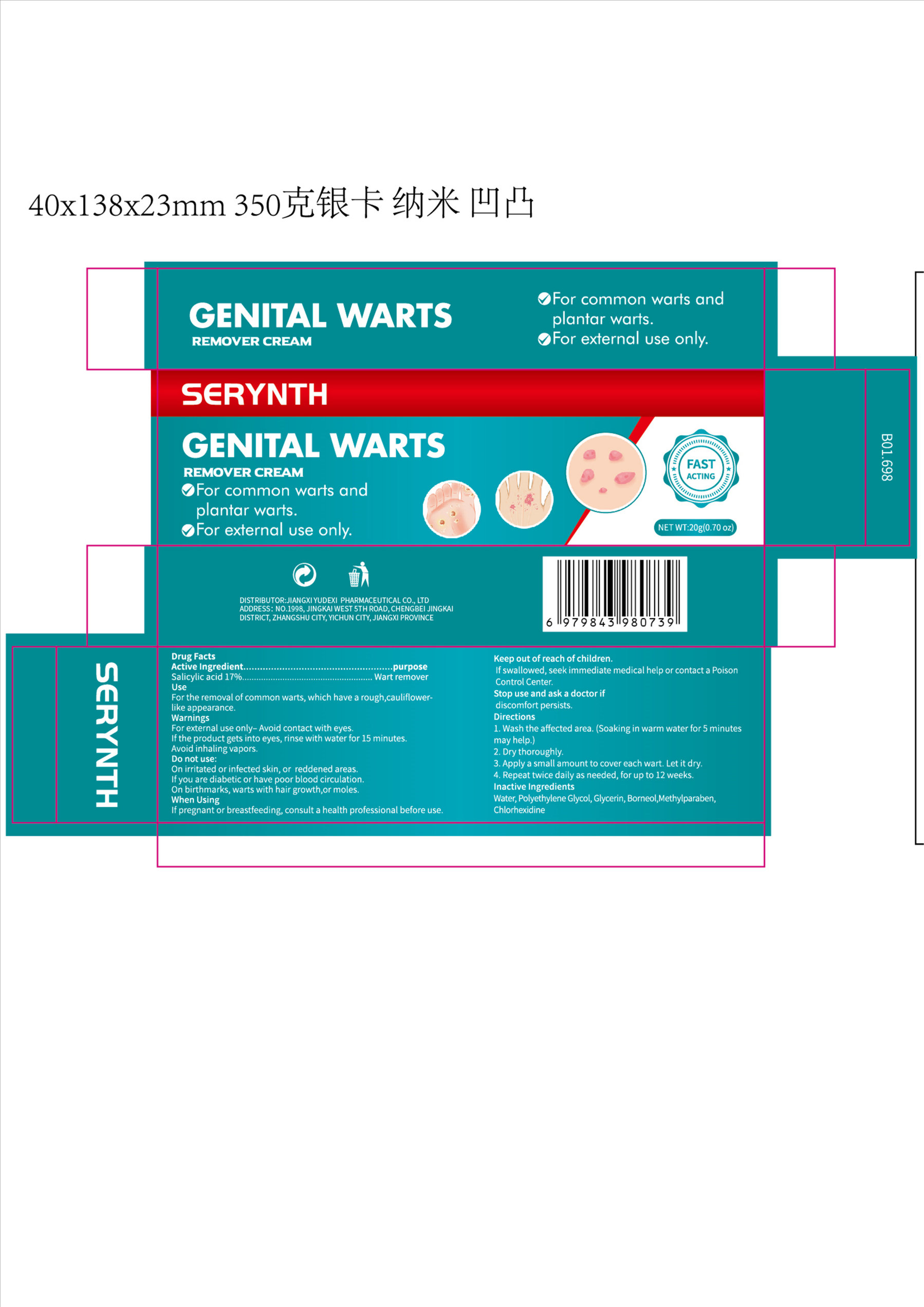 DRUG LABEL: SERYNTH GENITAL WARTS REMOVER
NDC: 85248-103 | Form: CREAM
Manufacturer: Jiangxi Yudexi Pharmaceutical Co., LTD
Category: otc | Type: HUMAN OTC DRUG LABEL
Date: 20260209

ACTIVE INGREDIENTS: SALICYLIC ACID 17 g/100 g
INACTIVE INGREDIENTS: BORNEOL; METHYLPARABEN; POLYETHYLENE GLYCOL, UNSPECIFIED; CHLORHEXIDINE; WATER; GLYCERIN

85248-103

Active Ingredient

Salicylic acid 17%

Purpose

Wart remover

Use

For the removal of common warts, which have a rough,cauliflower-like appearance.

Warnings

For external use only- Avoid contact with eyes. If the product gets into eyes, rinse with water for 15 minutes. Avoid inhaling vapors.

Do not use

On irritated or infected skin, or reddened areas. If you are diabetic or have poor blood circulation. On birthmarks, warts with hair growth,or moles.

When Using

If pregnant or breastfeeding, consult a health professional before use.

Stop Use

Stop use and ask a doctor if discomfort persists.

Ask Doctor

Stop use and ask a doctor if discomfort persists.

Keep Oot Of Reach Of Children

If swallowed, seek immediate Medical help or contact a poison Control center.

Directions

1.Wash the affected area.
(Soaking in warm water for 5 minutes may help.) 2. Dry thoroughly. 3. Apply a small amount to cover each wart. Let it dry 4. Repeat twice daily as needed, for up to 12 weeks.

Inactive ingredients

Water, polyethylene glycol, glycerin, borneol，methylparaben，chlorhexidine